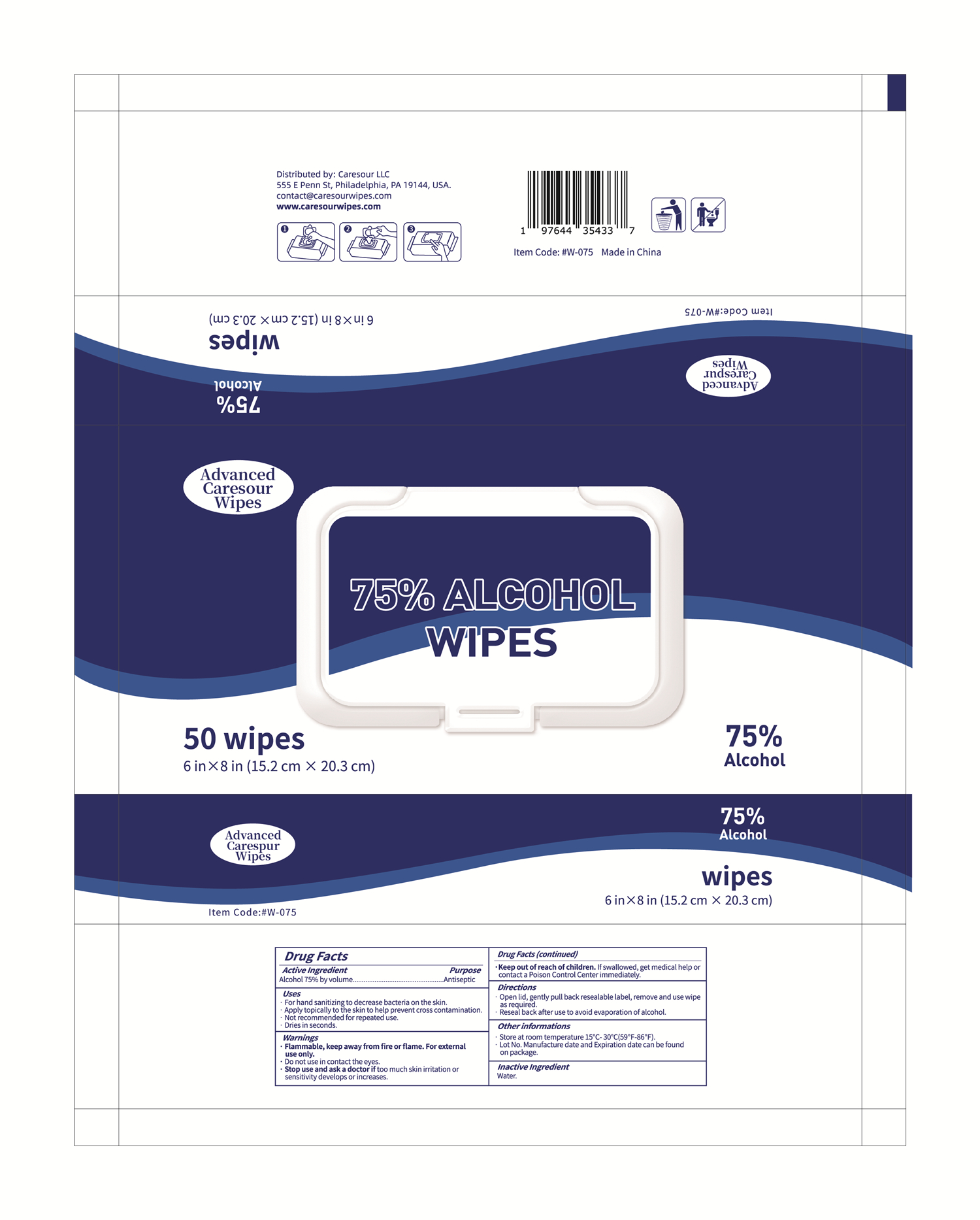 DRUG LABEL: Advanced Caresour Wipes
NDC: 83779-001 | Form: CLOTH
Manufacturer: Caresour LLC
Category: otc | Type: HUMAN OTC DRUG LABEL
Date: 20231029

ACTIVE INGREDIENTS: ALCOHOL 75 mL/100 mL
INACTIVE INGREDIENTS: WATER

83779-001 Advanced Caresour Wipes

Active Ingredient

Alcohol 75% by volume

Purpose

Antiseptic

Uses

· For hand sanitizing to decrease bacteria on the skin.

· Apply topically to the skin to help prevent cross contamination.

· Not recommended for repeated use.

· Dries in seconds.

Warnings

· Flammable, keep away from fire or flame. For external

use only.

· Do not use in contact the eyes.

· Stop use and ask a doctor if too much skin irritation or

sensitivity develops or increases.

·Keep out of reach of children. If swallowed, get medical help or

contact a Poison Control Center immediately.

Directions:

· Open lid, gently pull back resealable label, remove and use wipe

as required.

· Reseal back after use to avoid evaporation of alcohol.

STORAGE AND HANDLING

Other informations

· Store at room temperature 15℃- 30℃(59℉-86℉).

· Lot No. Manufacture date and Expiration date can be found

on package.

Inactive Ingredient

Water.

PACKAGE LABEL

50 wipes

NDC: 83779-001-01